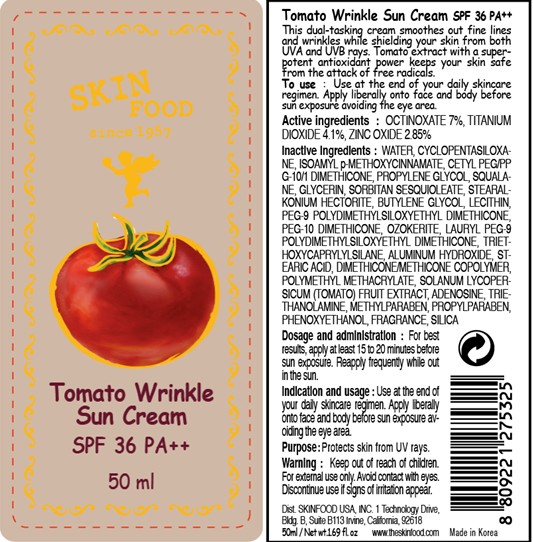 DRUG LABEL: TOMATO WRINKLE SUN
NDC: 76214-029 | Form: CREAM
Manufacturer: SKINFOOD CO., LTD.
Category: otc | Type: HUMAN OTC DRUG LABEL
Date: 20110929

ACTIVE INGREDIENTS: OCTINOXATE 3.5 mL/50 mL; TITANIUM DIOXIDE 2.05 mL/50 mL; ZINC OXIDE 1.43 mL/50 mL
INACTIVE INGREDIENTS: WATER; CYCLOMETHICONE 5; SILICON DIOXIDE; PROPYLENE GLYCOL; SQUALANE; GLYCERIN; SORBITAN SESQUIOLEATE; BUTYLENE GLYCOL; LECITHIN, SOYBEAN; TRIETHOXYCAPRYLYLSILANE; ALUMINUM HYDROXIDE; STEARIC ACID; METHYLPARABEN; PHENOXYETHANOL; PROPYLPARABEN; TOMATO; TROLAMINE; ADENOSINE

Drug Facts

ACTIVE INGREDIENT

Active ingredients: OCTINOXATE 7%, TITANIUM DIOXIDE 4.1%, ZINC OXIDE 2.85%

Inactive ingredients:
WATER, CYCLOPENTASILOXANE, ISOAMYL p-METHOXYCINNAMATE, CETYL PEG/PPG-10/1 DIMETHICONE, PROPYLENE GLYCOL, SQUALANE, GLYCERIN, SORBITAN SESQUIOLEATE, STEARALKONIUM HECTORITE, BUTYLENE GLYCOL, LECITHIN, PEG-9 POLYDIMETHYLSILOXYETHYL DIMETHICONE, PEG-10 DIMETHICONE, OZOKERITE, LAURYL PEG-9 POLYDIMETHYLSILOXYETHYL DIMETHICONE, TRIETHOXYCAPRYLYLSILANE, ALUMINUM HYDROXIDE, STEARIC ACID, DIMETHICONE/METHICONE COPOLYMER, POLYMETHYL METHACRYLATE, SOLANUM LYCOPERSICUM (TOMATO) FRUIT EXTRACT, ADENOSINE, TRIETHANOLAMINE, METHYLPARABEN, PROPYLPARABEN, PHENOXYETHANOL, FRAGRANCE, SILICA

Purpose: Protects skin from UV rays.

Warnings:
For external use only.
Avoid contact with eyes.
Discontinue use if signs of irritation appear.

Keep out of reach of children:
Keep out of reach of children.

Indication and usage:
Use at the end of your daily skincare regimen.
Apply liberally onto face and body before sun exposure avoiding the eye area.

Dosage and administration:
For best results, apply at least 15 to 20 minutes before sun exposure.
Reapply frequently while out in the sun.